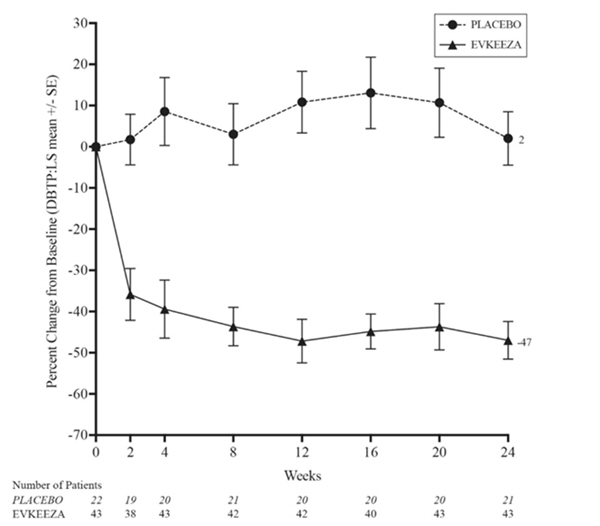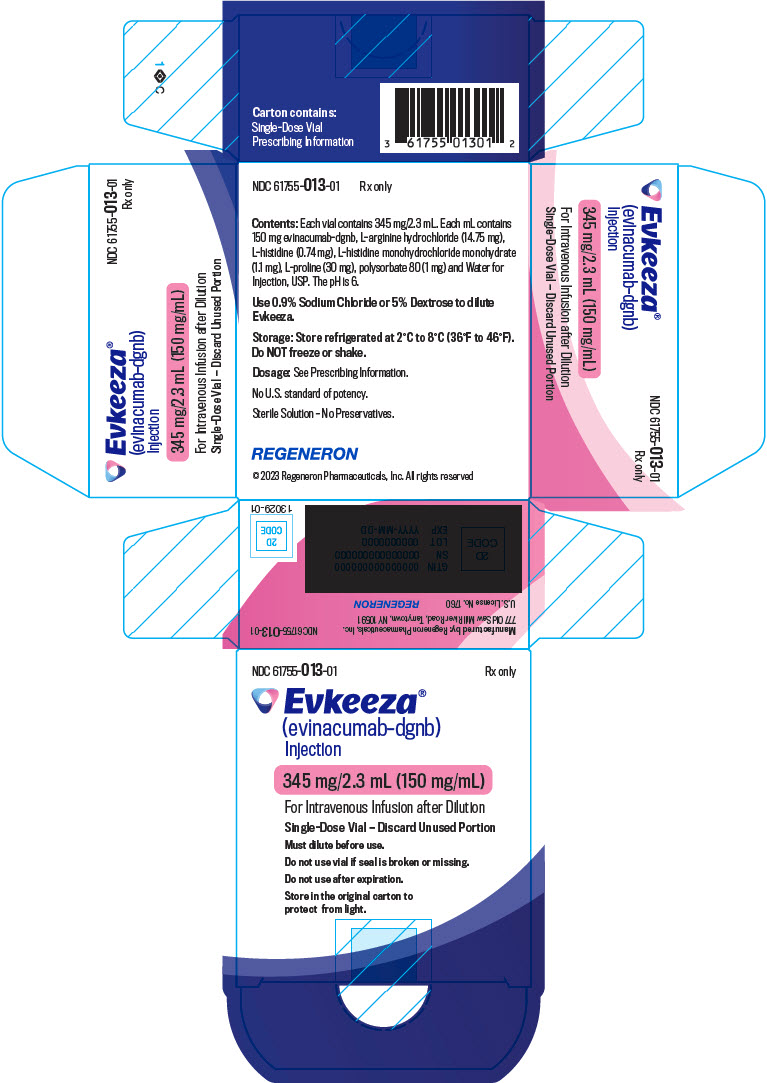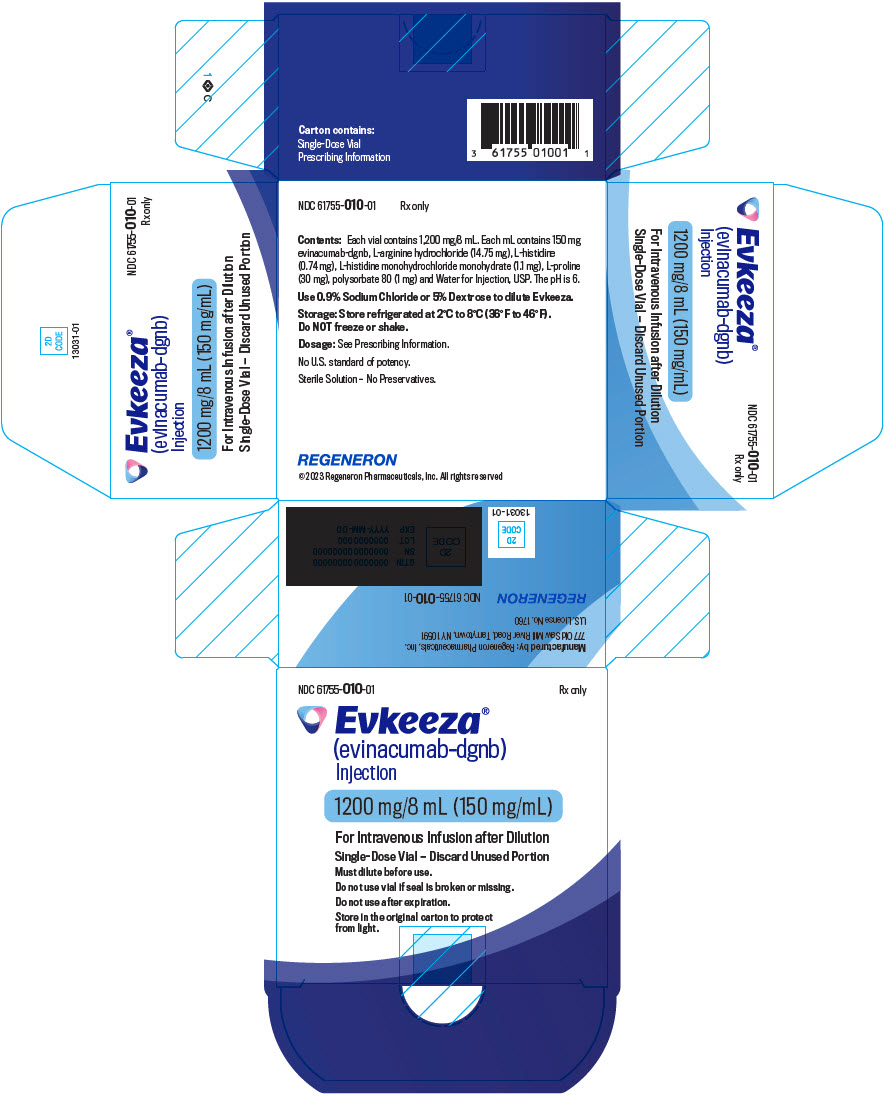 DRUG LABEL: Evkeeza
NDC: 61755-013 | Form: INJECTION, SOLUTION, CONCENTRATE
Manufacturer: Regeneron Pharmaceuticals, Inc.
Category: prescription | Type: HUMAN PRESCRIPTION DRUG LABEL
Date: 20250925

ACTIVE INGREDIENTS: evinacumab 150 mg/1 mL
INACTIVE INGREDIENTS: Histidine 0.74 mg/1 mL; Histidine monohydrochloride monohydrate 1.1 mg/1 mL; Proline 30 mg/1 mL; Polysorbate 80 1 mg/1 mL; Arginine hydrochloride 14.75 mg/1 mL; Water

HIGHLIGHTS OF PRESCRIBING INFORMATION

These highlights do not include all the information needed to use EVKEEZA safely and effectively. See full prescribing information for EVKEEZA.
EVKEEZA® (evinacumab-dgnb) injection, for intravenous use
Initial U.S. Approval: 2021

RECENT MAJOR CHANGES

Indications and Usage (1) | 9/2025
Dosage and Administration, Preparation Instructions of Intravenous Infusion (2.2) | 9/2025

1 INDICATIONS AND USAGE

EVKEEZA is an angiopoietin-like 3 (ANGPTL3) inhibitor indicated as an adjunct to diet and exercise and other low-density lipoprotein-cholesterol (LDL-C) lowering therapies to reduce LDL-C in adults and pediatric patients, aged 1 year and older, with homozygous familial hypercholesterolemia (HoFH). (1)

2 DOSAGE AND ADMINISTRATION

- The recommended dosage of EVKEEZA is 15 mg/kg administered by intravenous (IV) infusion once monthly (every 4 weeks). (2.1)
- See the Full Prescribing Information for preparation instructions for the intravenous infusion. (2.2)
- Administer the diluted solution via IV infusion over 60 minutes through an IV line containing a sterile, in-line or add-on, 0.2-micron to 5-micron filter. (2.3)
- Do not mix other medications with EVKEEZA or administer other medications concomitantly via the same infusion line. (2.3)
- The rate of infusion may be slowed, interrupted or discontinued if the patient develops any signs of adverse reactions, including infusion or hypersensitivity reactions. (2.3)

3 DOSAGE FORMS AND STRENGTHS

- Injection: 345 mg/2.3 mL (150 mg/mL) and 1,200 mg/8 mL (150 mg/mL) solution in single-dose vials. (3)

4 CONTRAINDICATIONS

- History of serious hypersensitivity reactions to evinacumab-dgnb or to any of the excipients in EVKEEZA. (4)

5 WARNINGS AND PRECAUTIONS

- Serious Hypersensitivity Reactions: Have occurred with EVKEEZA in clinical trials. If a serious hypersensitivity reaction occurs, discontinue EVKEEZA, treat according to standard-of-care and monitor until signs and symptoms resolve. (5.1)
- Embryo-Fetal Toxicity: EVKEEZA may cause fetal harm based on animal studies. Advise patients who may become pregnant of the risk to a fetus. Consider obtaining a pregnancy test prior to initiating treatment with EVKEEZA. Advise patients who may become pregnant to use contraception during treatment and for at least 5 months following the last dosage. (5.2, 8.1, 8.3)

6 ADVERSE REACTIONS

Common adverse reactions (≥5%) were nasopharyngitis, influenza-like illness, dizziness, rhinorrhea, nausea, and fatigue. (6.1)

To report SUSPECTED ADVERSE REACTIONS, contact Regeneron at 1-833-385-3392 or FDA at 1-800-FDA-1088 or www.fda.gov/medwatch.

FULL PRESCRIBING INFORMATION

1 INDICATIONS AND USAGE

EVKEEZA is indicated as an adjunct to diet and exercise and other low-density lipoprotein-cholesterol (LDL-C) lowering therapies to reduce LDL-C in adults and pediatric patients, aged 1 year and older, with homozygous familial hypercholesterolemia (HoFH).

2 DOSAGE AND ADMINISTRATION

2.1 Recommended Dosage

- The recommended dosage of EVKEEZA is 15 mg/kg administered by intravenous (IV) infusion over 60 minutes once monthly (every 4 weeks).
- If a dosage of EVKEEZA is missed, administer as soon as possible. Thereafter, EVKEEZA should be scheduled monthly from the date of the last dosage.
- Assess LDL-C when clinically appropriate. The LDL-lowering effect of EVKEEZA may be measured as early as 2 weeks after initiation.

2.2 Preparation Instructions for Intravenous Infusion

- Calculate the dosage (mg), total volume (mL) of EVKEEZA required, and the number of vials required based on the patient's current body weight.
- Visually inspect the solution for cloudiness, discoloration, and particulate matter prior to administration. EVKEEZA is a clear to slightly opalescent, colorless to pale-yellow solution. Do not administer if the solution is cloudy, discolored, or contains particulate matter.
- EVKEEZA is supplied as single-dose vials and does not contain a preservative. Prepare the diluted infusion using aseptic technique.
- Do not shake the vial. Withdraw the required volume from the vial(s) of EVKEEZA and transfer into an IV infusion bag of 0.9% Sodium Chloride Injection or 5% Dextrose Injection. Discard any unused portion left in the vials. Mix the diluted solution by gentle inversion; do not shake. Maximum diluent volume by patient weight is summarized in Table 1.
- Table 1: Maximum Diluent Volume by Patient Weight
  Patient Weight | Maximum Diluent Volume
  3 kg to less than 26 kg | 5 mL/kg
  26 kg to less than 45 kg | 150 mL
  45 kg and greater | 250 mL
- The final concentration of the diluted solution should be between 0.5 mg/mL and 20 mg/mL depending on the patient's current body weight.
- Administer the diluted solution immediately after preparation and discard any unused portion left in the vial.
- If not administered immediately, store the diluted solution refrigerated at 2 °C to 8 °C (36 °F to 46 °F) for no more than 24 hours from the time of preparation OR at room temperature up to 25 °C (77 °F) for no more than 6 hours from the time of preparation to the end of the infusion. Do not freeze the diluted solution.

2.3 Administration Instructions for Intravenous Infusion

- If refrigerated, allow the diluted solution to come to room temperature prior to administration.
- Administer EVKEEZA diluted solution via IV infusion through an IV line containing a sterile, in-line or add-on, 0.2-micron to 5-micron filter over 60 minutes.
- Do not mix other medications with EVKEEZA or administer other medications concomitantly via the same infusion line.
- The rate of infusion may be slowed, interrupted or discontinued if the patient develops any signs of adverse reactions, including infusion or hypersensitivity reactions [see Warnings and Precautions (5.1) and Adverse Reactions (6.1)].
- EVKEEZA can be administered without regard to the timing of lipoprotein apheresis.

3 DOSAGE FORMS AND STRENGTHS

EVKEEZA is a clear to slightly opalescent, colorless to pale yellow solution available as follows:

- Injection: 345 mg/2.3 mL (150 mg/mL) and 1,200 mg/8 mL (150 mg/mL) in single-dose vials.

4 CONTRAINDICATIONS

EVKEEZA is contraindicated in patients with a history of serious hypersensitivity reaction to evinacumab-dgnb or to any of the excipients in EVKEEZA. Serious hypersensitivity reactions, including anaphylaxis, have occurred [see Warnings and Precautions (5.1)].

5 WARNINGS AND PRECAUTIONS

5.1 Serious Hypersensitivity Reactions

Serious hypersensitivity reactions, including anaphylaxis, have occurred with EVKEEZA [see Adverse Reactions (6.1)]. If signs or symptoms of serious hypersensitivity reactions occur, discontinue EVKEEZA infusion, treat according to the standard-of-care, and monitor until signs and symptoms resolve. EVKEEZA is contraindicated in patients with a history of serious hypersensitivity reaction to evinacumab-dgnb.

5.2 Embryo-Fetal Toxicity

Based on the findings in animal reproduction studies, EVKEEZA may cause fetal harm when administered to pregnant patients. Administration of evinacumab-dgnb to rabbits during organogenesis caused increases in fetal malformations at doses below the human exposure. Advise patients who may become pregnant of the risk to a fetus. Consider obtaining a pregnancy test prior to initiating treatment with EVKEEZA. Advise patients who may become pregnant to use effective contraception during treatment with EVKEEZA and for at least 5 months following the last dosage of EVKEEZA [see Use in Specific Populations (8.1, 8.3)].

6 ADVERSE REACTIONS

The following clinically significant adverse reactions are described elsewhere in the labeling:

- Serious Hypersensitivity Reactions [see Warnings and Precautions (5.1)]

6.1 Clinical Trials Experience

Because clinical trials are conducted under widely varying conditions, adverse reaction rates observed in the clinical trials of a drug cannot be directly compared to rates in the clinical trials of another drug and may not reflect the rates observed in practice.

Adverse Reactions in Adult and Pediatric Patients (aged 12 to 17 years) with HoFH

Safety data are based on pooled results from two randomized, double-blind, placebo-controlled trials that included 81 patients treated with EVKEEZA. The mean age of EVKEEZA-treated patients was 48 years (range: 15 to 75 years); 52% were females; 5% were Hispanic; 82% were White, 7% Asian, 3% Black or African American, and 9% other races. Forty-four (54%) EVKEEZA-treated patients had HoFH. Patients received EVKEEZA as add-on therapy to other lipid-lowering therapies, including maximally tolerated statin, ezetimibe, proprotein convertase subtilisin kexin type 9 (PCSK9) inhibitors, lomitapide, and apheresis.

Adverse reactions led to discontinuation of treatment in 1 (2%) patient who received placebo, and 2 (2%) patients treated with EVKEEZA, including 1 case of anaphylaxis. The most common adverse reactions (reported in greater than 3% of EVKEEZA-treated patients and more frequently than in placebo) are shown in Table 2.

Table 2: Adverse Reactions Occurring in >3% of Adult and Pediatric Patients Aged 12 to 17 Years Treated with EVKEEZA and Greater than Placebo in 24-Week, Pooled, Placebo-Controlled Trials
Adverse Reactions | Placebo (N = 54) % | EVKEEZA (N = 81) %
Nasopharyngitis | 13 | 16
Influenza like illness | 6 | 7
Dizziness | 0 | 6
Rhinorrhea | 0 | 5
Nausea | 2 | 5
Pain in extremity | 0 | 4
Asthenia | 0 | 4

Other adverse reactions occurring in less than 3% of patients treated with EVKEEZA and greater than placebo included constipation, upper respiratory tract infection, nasal congestion, and abdominal pain.

Transient, mild to moderate decreases in diastolic blood pressure and increases in heart rate occurred in clinical trials of EVKEEZA infusion but did not require intervention and resolved post-infusion.

Serious Hypersensitivity Reactions

Anaphylaxis was reported in 0% patients who received placebo and 1 (1%) patient treated with EVKEEZA.

Infusion Reactions

Infusion reactions were reported in 2 (4%) patients who received placebo and 6 (7%) patients treated with EVKEEZA. The following infusion reactions occurred in EVKEEZA-treated patients: infusion site pruritus, pyrexia, muscular weakness, nausea, and nasal congestion.

Adverse Reactions in Pediatric Patients (aged 5 to 11 years) with HoFH

Safety data are based on pooled results from a three-part, open-label trial in 20 pediatric patients with HoFH (aged 5 to 11 years) with a median treatment duration of 50 weeks. Part A was a trial of 6 patients who received a single intravenous dose of EVKEEZA 15 mg/kg to determine the dosage for the rest of the trial. Part B was a single-arm, 24-week trial of EVKEEZA 15 mg/kg given intravenously every 4 weeks in 14 unique patients [see Clinical Studies (14)]. Part C was a 48-week extension trial of EVKEEZA 15 mg/kg given intravenously every 4 weeks that consisted of 20 patients who entered directly from Parts A or B. The mean age was 9 years (range: 5 to 11 years); 60% females; 70% White, 10% Asian, 5% Black or African American, 5% American Indian or Alaska Native, and 10% other races. The safety profile of EVKEEZA observed in these patients was consistent with the safety profile observed in adults and pediatric patients aged 12 years and older, with the additional adverse reaction of fatigue. Fatigue was reported in 3 (15%) patients.

8 USE IN SPECIFIC POPULATIONS

8.1 Pregnancy

Risk Summary

Based on data from animal reproduction studies, EVKEEZA may cause fetal harm when administered to pregnant patients. Available human data are insufficient to evaluate for a drug-associated risk of major birth defects, miscarriage or adverse maternal or fetal outcomes. Evinacumab-dgnb is a human IgG4 monoclonal antibody [see Description (11)], and human IgG is known to cross the placental barrier; therefore, evinacumab-dgnb has the potential to be transmitted from the mother to the developing fetus.

Subcutaneous administration of evinacumab-dgnb to pregnant rabbits during the period of organogenesis resulted in fetal malformations (domed head, hydrocephalus, and flexed limbs) at doses below the maximum recommended human dose (MRHD). No adverse embryofetal effects were observed with subcutaneous administration of evinacumab-dgnb to pregnant rats during the period of organogenesis at doses below the MRHD. Measurable evinacumab-dgnb serum concentrations were observed in fetal rabbit and rat sera at birth, indicating that evinacumab-dgnb, like other IgG antibodies, crosses the placental barrier (see Data). Advise pregnant women of the potential risk to a fetus.

The estimated background risk of major birth defects and miscarriage for the indicated population are unknown. In the U.S. general population, the estimated background risk of major birth defects and miscarriage in clinically recognized pregnancies is 2-4% and 15-20%, respectively.

If a patient becomes pregnant while receiving EVKEEZA, healthcare providers should report EVKEEZA exposure by calling 1-833-385-3392.

Data

Animal Data

In an embryo-fetal development study in pregnant rabbits, evinacumab-dgnb was administered subcutaneously at doses of 1, 5, 10 and 30 mg/kg every 3 days (Q3D) during the period of organogenesis from gestation day 7 to day 19. Evinacumab-dgnb was teratogenic in rabbits, causing domed head, dilation of the lateral and third ventricles of the brain, and flexed fore/hind paws at maternal evinacumab-dgnb exposures below human exposure at the MRHD of 15 mg/kg every 4 weeks, based on AUC. Other fetal malformations, consisting of irregular and abnormal ossification in the skull, palate, and metacarpal, and enlarged anterior and/or posterior fontanelles occurred and were consistent with significant maternal toxicity (including early deaths due to abortion and premature delivery at all doses, reduction in maternal body weight gains, and reduced maternal food consumption). Increased incidences of post-implantation losses, resorptions (total, early, and late), and decreased fetal body weight were also consistent with maternal toxicity. Evinacumab-dgnb was present in the sera of fetuses born from mothers at 10 and 30 mg/kg/Q3D at levels higher than in maternal serum.

In an embryo-fetal development study in pregnant rats, evinacumab-dgnb was administered subcutaneously at doses of 5, 10, 30 and 100 mg/kg/Q3D during the period of organogenesis from gestation day 6 to day 18. Maternal exposures to evinacumab-dgnb were below the human exposure measured at the MRHD. Evinacumab-dgnb resulted in unexplained maternal deaths at 100 mg/kg/Q3D. Evinacumab-dgnb crossed the placenta and was present at ratios (CFetal/CMaternal) ranging from 0.42 to 0.65. No adverse effects on embryofetal development were observed at any dose.

In a combined fertility, embryofetal, and pre- and postnatal development study, female rats were administered evinacumab-dgnb via subcutaneous injection at doses of 30 and 100 mg/kg/Q3D beginning 2 weeks prior to mating and continuing to gestation day 21 or lactation day 21. Mean maternal systemic exposures were below the human exposure at the MRHD throughout the study. No maternal or developmental toxicity was observed.

8.2 Lactation

Risk Summary

There are no data on the presence of evinacumab-dgnb in human milk or animal milk, the effects on the breastfed infant, or the effects on milk production. Maternal IgG is known to be present in human milk. The effects of local gastrointestinal exposure and limited systemic exposure in the breastfed infant to evinacumab-dgnb are unknown. The developmental and health benefits of breastfeeding should be considered along with the mother's clinical need for EVKEEZA and any potential adverse effects on the breastfed infant from EVKEEZA or from the underlying maternal condition.

8.3 Females and Males of Reproductive Potential

Pregnancy Testing

Consider pregnancy testing in patients who may become pregnant prior to starting treatment with EVKEEZA [see Warnings and Precautions (5.2) and Use in Specific Populations (8.1)].

Contraception

Females

Based on animal studies, EVKEEZA may cause fetal harm when administered to pregnant patients [see Use in Specific Populations (8.1)]. Patients who may become pregnant should use effective contraception during treatment with EVKEEZA and for at least 5 months following the last dosage of EVKEEZA.

8.4 Pediatric Use

The safety and effectiveness of EVKEEZA as an adjunct to other LDL-C-lowering therapies for the treatment of HoFH have been established in pediatric patients aged 1 year and older. Use of EVKEEZA for this indication is supported by evidence from adequate and well-controlled trials in adults with additional pharmacokinetic, efficacy, and safety data in pediatric patients aged 1 year and older [see Adverse Reactions (6.1), Clinical Pharmacology (12.3) and Clinical Studies (14)]. The safety profile of EVKEEZA in pediatric patients aged 1 to 11 years was similar to the safety profile in adults and pediatric patients aged 12 years and older, with the additional adverse reaction of fatigue in patients aged 5 to 11 years [see Adverse Reactions (6.1)].

The safety and effectiveness of EVKEEZA have not been established in pediatric patients younger than 1 year of age.

8.5 Geriatric Use

Clinical studies of EVKEEZA did not include sufficient numbers of patients 65 years of age and older to determine whether they respond differently from younger adult patients.

11 DESCRIPTION

Evinacumab-dgnb is an angiopoietin-like protein 3 (ANGPTL3) inhibitor monoclonal antibody (IgG4 isotype) produced by recombinant DNA technology in Chinese hamster ovary (CHO) cell suspension culture. Evinacumab-dgnb has an approximate molecular weight of 146 kDa.

EVKEEZA (evinacumab-dgnb) injection is a sterile, preservative-free solution for intravenous use. The solution is clear to slightly opalescent, colorless to pale-yellow, and free from visible particles.

Each vial contains 345 mg/2.3 mL or 1,200 mg/8 mL. Each mL contains 150 mg of evinacumab-dgnb, and L-arginine hydrochloride (14.8 mg), L-histidine (0.74 mg), L-histidine monohydrochloride monohydrate (1.1 mg), L-proline (30 mg), polysorbate 80 (1 mg) and Water for Injection, USP. The pH is 6.

12 CLINICAL PHARMACOLOGY

12.1 Mechanism of Action

Evinacumab-dgnb is a recombinant human monoclonal antibody that binds to and inhibits ANGPTL3. ANGPTL3 is a member of the angiopoietin-like protein family that is expressed primarily in the liver and plays a role in the regulation of lipid metabolism by inhibiting lipoprotein lipase (LPL) and endothelial lipase (EL). Evinacumab-dgnb inhibition of ANGPTL3 leads to reduction in LDL-C, high-density lipoprotein cholesterol (HDL-C), and triglycerides (TG). Evinacumab-dgnb reduces LDL-C independent of the presence of LDL receptor (LDLR) by promoting very low-density lipoprotein (VLDL) processing and clearance upstream of LDL formation. Evinacumab-dgnb blockade of ANGPTL3 lowers TG and HDL-C by rescuing LPL and EL activities, respectively.

12.2 Pharmacodynamics

Administration of evinacumab-dgnb in patients with HoFH resulted in reductions in LDL-C, total cholesterol (TC), HDL-C, apolipoprotein B and TG [see Clinical Studies (14)].

12.3 Pharmacokinetics

The pharmacokinetic parameters described in this section are presented following administration of evinacumab-dgnb 15 mg/kg intravenously every 4 weeks, unless otherwise specified.

Steady-state is reached after 4 doses, and the accumulation ratio is 2. According to population pharmacokinetic modeling, the mean (standard deviation) steady-state trough concentration is 266 (120) mg/L in adult patients, whereas the mean (standard deviation) Cmax at the end of infusion is 718 (183) mg/L in adult patients. Due to non-linear clearance, a 4.3-fold increase in area under the concentration-time curve at steady-state (AUCtau.ss) for a 3-fold increase in evinacumab-dgnb dose up to 15 mg/kg IV every 4 weeks was predicted in patients with HoFH.

Distribution

The steady-state volume of distribution estimated via population pharmacokinetic analysis was approximately 4.7 L in adult patients.

Elimination

Evinacumab-dgnb elimination is mediated via parallel linear and non-linear pathways. At higher concentrations, evinacumab-dgnb elimination is primarily through a non-saturable proteolytic pathway, whereas at lower concentrations, the non-linear, saturable ANGPTL3 target-mediated elimination predominates. The elimination half-life is a function of serum evinacumab-dgnb concentrations and is not a constant.

Based on a population pharmacokinetic analysis, the median time for serum evinacumab-dgnb concentrations to decrease below the lower limit of quantitation (78 ng/mL) is approximately 20 weeks after the last steady-state dose of 15 mg/kg IV every 4 weeks.

Metabolism

The exact pathway through which evinacumab-dgnb is metabolized has not been characterized. As a human monoclonal IgG4 antibody, evinacumab-dgnb is expected to be degraded into small peptides and amino acids via catabolic pathways in the same manner as endogenous IgG.

Excretion

Evinacumab-dgnb, a monoclonal antibody, is not likely to undergo renal excretion.

Specific Populations

A population PK analysis conducted on data from 183 healthy subjects and 139 patients with HoFH suggests that the following factors have no clinically significant effect on the exposure of evinacumab-dgnb: age (5 to 75 years), gender, body weight (20 to 152 kg), and race (White, Asian, Black or African American, American Indian or Alaska Native, and other races).

Pediatric Patients

Fourteen (14) patients aged 12 to less than 18 years with HoFH received evinacumab-dgnb at 15 mg/kg IV every 4 weeks. Steady-state trough and end-of-infusion concentrations were within the range observed in adult patients.

Twenty (20) patients aged 5 to less than 12 years with HoFH received evinacumab-dgnb at 15 mg/kg IV every 4 weeks. According to population pharmacokinetic modeling, the mean (standard deviation) steady-state trough concentration is 160 (57.6) mg/L in pediatric patients, whereas the mean (standard deviation) Cmax at the end of infusion is 419 (99.4) mg/L in pediatric patients. Steady-state trough and end-of-infusion concentrations were lower but within the range observed in adult patients.

The predicted mean (standard deviation) steady-state trough and maximum concentrations were 135 (62) and 500(182) mg/L for patients aged 1 year to less than 2 years. The predicted mean (standard deviation) steady-state trough and maximum concentrations were 141(61) and 513(179) mg/L for patients aged 2 to less than 5 years.

Patients with Renal Impairment

Observed trough serum evinacumab-dgnb concentrations at steady-state were comparable between patients with mild or moderate renal impairment and patients with normal renal function. No data are available in patients with severe renal impairment.

Patients with Hepatic Impairment

No data are available in patients with hepatic impairment.

Drug Interaction Studies

Drug interaction studies have not been conducted with evinacumab-dgnb. In a clinical trial, the concentrations of statins (atorvastatin, rosuvastatin, simvastatin) were not meaningfully altered in patients taking statins prior to and post administration of evinacumab-dgnb. Concentrations of evinacumab-dgnb were comparable in patients with HoFH taking or not taking background lipid-lowering therapy.

12.6 Immunogenicity

The observed incidence of anti-drug antibodies is highly dependent on the sensitivity and specificity of the assay. Differences in assay methods preclude meaningful comparisons of the incidence of anti-drug antibodies in the trials described below with the incidence of anti-drug antibodies in other trials, including those of EVKEEZA or of other evinacumab-dgnb products. During the 24-week treatment period in the trials in:

- Adult and pediatric patients aged 12 years and older with HoFH (Trials 1 and 2) [see Clinical Studies (14)], the incidence of anti-evinacumab-dgnb antibody formation was 0% (0 of 56) in EVKEEZA-treated patients.
- Pediatric patients aged 5 to 11 years with HoFH (Trial 3) [see Clinical Studies (14)], the incidence of anti-evinacumab-dgnb antibody formation was 5% (1 of 20) in EVKEEZA-treated patients. In the one patient that developed anti-evinacumab-dgnb antibodies, there were no effects on efficacy or evinacumab-dgnb concentrations.
- Because of the low occurrence of anti-evinacumab-dgnb antibodies, the effect of these antibodies on the pharmacokinetics, pharmacodynamics, safety, and/or effectiveness of evinacumab products is unknown.

13 NONCLINICAL TOXICOLOGY

13.1 Carcinogenesis, Mutagenesis, Impairment of Fertility

Carcinogenesis and Mutagenesis

Carcinogenicity studies have not been conducted with evinacumab-dgnb. The mutagenic potential of evinacumab-dgnb has not been evaluated; however, monoclonal antibodies are not expected to alter DNA or chromosomes.

Impairment of Fertility

There were no adverse effects on surrogate markers of fertility (estrous cyclicity, testicular volume, ejaculate volume, sperm motility, total sperm count per ejaculate, and histology of reproductive organs) in a 6-month chronic toxicology study in sexually-mature male and female monkeys subcutaneously administered 10, 30, or 100 mg/kg/week (0.2, 1, and 3-fold MRHD based on AUC, respectively) and intravenously administered 100 mg/kg/week (4-fold MRHD, based on AUC).

In a combined fertility and early embryonic and pre-and postnatal development study in female rats administered evinacumab-dgnb via subcutaneous injection at dosages 30 and 100 mg/kg/Q3D beginning 2 weeks prior to mating, no adverse effect on female fertility were observed at any dosage. Exposures to evinacumab-dgnb represented less than the human exposure at the MRHD, based on AUC. No effects on male fertility were observed with evinacumab-dgnb administration to male rabbits for 40 days prior to mating with treatment-naïve females. Evinacumab-dgnb was administered to male rabbits intravenously at 100 and 300 mg/kg/Q5D, representing exposures 2- and 5-times, respectively, the human exposure at the MRHD, based on AUC.

14 CLINICAL STUDIES

Adult and Pediatric Patients Aged 12 Years and Older with HoFH

Trial ELIPSE-HoFH (NCT03399786; Trial 1) was a multicenter, double-blind, randomized, placebo-controlled trial that evaluated the efficacy of EVKEEZA compared to placebo in 65 patients with HoFH (63 adult patients and 2 pediatric patients). During the 24-week, double-blind treatment period, patients were randomized to receive EVKEEZA 15 mg/kg given intravenously every 4 weeks (n=43) or placebo given intravenously every 4 weeks (n=22). After the double-blind treatment period, 64 of 65 patients entered a 24-week open-label extension period in which all patients received EVKEEZA 15 mg/kg given intravenously every 4 weeks.

Patients were on a background of other lipid-lowering therapies, including maximally tolerated statins, ezetimibe, PCSK9 inhibitor antibodies, lomitapide, and lipoprotein apheresis. Enrollment was stratified by apheresis status and geographical region. The diagnosis of HoFH was determined by genetic testing or by the presence of the following clinical criteria: history of an untreated total cholesterol (TC) >500 mg/dL and either xanthoma before 10 years of age or evidence of TC >250 mg/dL in both parents.

Baseline Disease and Demographic Characteristics

In this trial, 40% (26 of 65) patients had limited LDL receptor (LDLR) function, defined by either <15% receptor function by in vitro assays or by genetic variants likely to result in minimal to no LDLR function by mutation analysis.

The mean LDL-C at baseline was 255 mg/dL (in patients with limited LDLR function, the mean LDL-C at baseline was 307 mg/dL). At baseline, 94% of patients were on statins, 75% on ezetimibe, 77% on a PCSK9 inhibitor antibody, 22% on lomitapide, and 34% were receiving lipoprotein apheresis. The mean age at baseline was 42 years (range 12 to 75) with 12% ≥65 years old; 54% females; 3% Hispanic; 74% White, 15% Asian, 3% Black or African American, and 8% other races or race was not reported.

Endpoint Results

The primary efficacy endpoint was percent change in LDL-C from baseline to Week 24. At Week 24, the least squares (LS) mean treatment difference between the EVKEEZA and placebo groups in mean percent change in LDL-C from baseline was −49% (95% confidence interval: −65% to −33%; p <0.0001). After 24 weeks of open-label EVKEEZA treatment (Week 24 to Week 48), the observed LDL-C reduction from baseline was similar in patients who crossed over from placebo to EVKEEZA and was maintained in patients who remained on EVKEEZA for 48 weeks. For efficacy results see Table 3.

At Week 24, the observed reduction in LDL-C with EVKEEZA was similar across predefined subgroups, including age, sex, limited LDLR activity, concomitant treatment with lipoprotein apheresis, and concomitant background lipid-lowering medications (statins, ezetimibe, PCSK9 inhibitor antibodies, and lomitapide).

Table 3: Lipid Parameters in Patients (63 Adults and 2 Pediatric Patients) with HoFH on Other Lipid-Lowering Therapies in Trial ELIPSE-HoFH (Trial 1)
 | LDL-C | ApoB | Non-HDL-C | TC | TG [Neither TG nor HDL-C were pre-specified in the hypothesis testing] | HDL-C
Baseline (mean), mg/dL (N=65) | 255 | 171 | 278 | 322 | 124 | 44
LS Mean: EVKEEZA (N = 43) | −47% | −41% | −50% | −47% | −55% | −30% [Mean percent change, based on safety population (EVKEEZA, n=44; placebo, n=21); HDL-C is presented for completeness but was not an efficacy endpoint that was statistically analyzed.]
LS Mean: Placebo (N = 22) | +2% | −5% | +2% | +1% | −5% | +1%
LS Mean Difference from Placebo (95% CI) | −49% (−65 to −33) | −37% (−49 to −25) | −52% (−65 to −39) | −48% (−59 to −38) | −50% (−66 to −35) | ^-
One subject in the placebo group discontinued the trial before Week 24. The treatment difference and 95% confidence interval (CI) were estimated using a mixed model repeated measures analysis.
Abbreviations: HoFH=homozygous familial hypercholesterolemia, ITT=intent-to-treat, LS mean=least squares mean, N=number of randomized patients, CI=confidence interval

The LS mean LDL-C percent changes over time are presented in Figure 1.

Figure 1: Calculated LDL-C LS Mean Percent Change from Baseline Over Time Through Week 24 in Patients (63 Adults and 2 Pediatric Patients) with HoFH in Trial ELIPSE-HoFH (Trial 1)

Abbreviations: LS mean=least squares mean, HoFH=homozygous familial hypercholesterolemia, DBTP=double-blind treatment period, SE=standard error

Pediatric Patients (aged 12 to 17 years) with HoFH

In an open-label trial (Trial 2), 13 pediatric patients with HoFH (aged 12 to 17 years) received 15 mg/kg of EVKEEZA given intravenously every 4 weeks as an adjunct to other lipid-lowering therapies (e.g., statins, ezetimibe, PCSK9 inhibitor antibodies and lipoprotein apheresis) for a median treatment duration of 33 weeks. The mean percent change from baseline in LDL-C at Week 24 was −52% in the 9 patients who completed treatment and had a lipid assessment at Week 24. Overall, the effect of EVKEEZA on lipid parameters in pediatric patients aged 12 to 17 years with HoFH was generally similar to that seen in adults with HoFH.

Pediatric Patients (aged 5 to 11 years) with HoFH

Trial R1500-CL-17100 (NCT04233918; Trial 3) was a multicenter, three-part, single-arm, open-label trial in pediatric patients aged 5 to 11 years with HoFH [see Adverse Reactions (6.1)]. Part B of this trial evaluated the efficacy of EVKEEZA 15 mg/kg given intravenously every 4 weeks as an adjunct to other lipid-lowering therapies (e.g., statins, ezetimibe, lomitapide, and lipoprotein apheresis) for 24 weeks in 14 patients with HoFH.

Baseline Disease and Demographic Characteristics

In Part B, the mean LDL-C at baseline was 264 mg/dL.

At baseline, 86% of patients were on statins, 93% on ezetimibe, 14% on lomitapide, and 50% were receiving lipoprotein apheresis.

The mean age at baseline was 9 years (range 5 to 11); 57% females; 0% Hispanic; 57% White, 14% Asian, 7% Black or African American, 7% American Indian or Alaska Native, and 14% other races. Mean body weight was 40 kg. Body mass index (BMI) was 20 kg/m^2.

Endpoint Results

The primary efficacy endpoint was percent change in calculated LDL-C from baseline to Week 24. At Week 24, the mean percent change in calculated LDL-C from baseline was −48% (95% confidence interval: −69% to −28%). For efficacy results see Table 4. HDL-C and TG reductions observed in this trial were similar to changes seen in Trial 1, see Table 3.

At Week 24, the reduction in LDL-C with EVKEEZA was similar across baseline characteristics, including age, sex, limited LDLR activity, concomitant treatment with lipoprotein apheresis, and concomitant background lipid-lowering medications (statins, ezetimibe, and lomitapide).

Table 4: Lipid Parameters in EVKEEZA-Treated Pediatric Patients (aged 5 to 11 years) with HoFH Who Received Concomitant Lipid-Lowering Therapies (Trial 3)
 | LDL-C | ApoB | Non-HDL-C | TC
Baseline (mean) (N=14) | 264 mg/dL | 168 mg/dL | 282 mg/dL | 316 mg/dL
Percent Change from Baseline at Week 24 (95% CI) | -48 (-69 to -28) | -41 (-59 to -24) | -49 (-68 to -30) | -49 (-65 to -33)
Abbreviations: HoFH=homozygous familial hypercholesterolemia, N=number of randomized patients, CI=confidence interval

Pediatric Patients (aged 1 to less than 5 years) with HoFH

Clinical data were collected through an expanded access program that required each patient's treating physician to provide adequate documentation to demonstrate that the patient met the eligibility criteria for the program and to provide effectiveness information, including LDL-C values. The efficacy of EVKEEZA was evaluated in 6 patients aged 1 to less than 5 years with HoFH. Four females and two males were enrolled in the program. At baseline, 83% of patients were on statins, 83% on ezetimibe, 17% on PCSK9 inhibitors, and 17% were receiving plasmapheresis. The mean LDL-C at baseline was 499 mg/dL (range 238 to 872 mg/dL), the mean age was 3.2 years (range 1.1 to 4.4 years), and the mean weight was 14.5 kg (range 8 to 17 kg). Patients received 15 mg/kg EVKEEZA every 4 weeks for up to 98 weeks. Administration of EVKEEZA resulted in a reduction of LDL-C [mean (standard deviation) change at Week 40 of -60% (16.8)].

16 HOW SUPPLIED/STORAGE AND HANDLING

EVKEEZA (evinacumab-dgnb) injection is a clear to slightly opalescent, colorless to pale yellow solution. It is supplied as one single-dose vial per carton.

- 345 mg/2.3 mL (150 mg/mL) NDC 61755-013-01
- 1,200 mg/8 mL (150 mg/mL) NDC 61755-010-01

Storage

Store in a refrigerator at 2 °C to 8 °C (36 °F to 46 °F). Store the vial in the original carton to protect from light. Do not freeze. Do not shake.

EVKEEZA does not contain a preservative. If not used immediately, store the diluted solution refrigerated at 2 °C to 8 °C (36 °F to 46 °F) for no more than 24 hours from the time of preparation OR at room temperature up to 25 °C (77 °F) for no more than 6 hours from the time of infusion preparation to the end of the infusion [see Dosage and Administration (2.2)].

17 PATIENT COUNSELING INFORMATION

Advise the patient to read the FDA-approved patient labeling (Patient Information).

Hypersensitivity Reactions

Inform patients that hypersensitivity reactions have occurred with EVKEEZA. Advise patients to contact their healthcare provider immediately if they experience signs or symptoms of a hypersensitivity reaction [see Warnings and Precautions (5.1)].

Embryofetal Toxicity

Advise pregnant patients and patients that may become pregnant of the potential risk to a fetus and to inform their healthcare provider of a known or suspected pregnancy. Advise patients who may become pregnant to use effective contraception during treatment with EVKEEZA and for 5 months after the final dosage. Encourage patients who become pregnant to report their pregnancy to 1-833-385-3392 [see Warnings and Precautions (5.2) and Use in Specific Populations (8.1, 8.3)].

Manufactured by:

Regeneron Pharmaceuticals, Inc.
777 Old Saw Mill River Road
Tarrytown, NY 10591-6707
U.S. License No. 1760
EVKEEZA is a registered trademark of Regeneron Pharmaceuticals, Inc.
All rights reserved.
©2025, Regeneron Pharmaceuticals, Inc.

Patient Information
EVKEEZA® (ev-kee'-zah)
(evinacumab-dgnb)
injection, for intravenous use

What is EVKEEZA?
EVKEEZA is an injectable prescription medicine used along with diet and exercise and other low-density lipoprotein cholesterol (LDL-C) lowering medicines to lower LDL-C in adults and children 1 year of age and older with a type of high cholesterol called homozygous familial hypercholesterolemia (HoFH).

It is not known if EVKEEZA is safe and effective in children under 1 year of age.

Who should not use EVKEEZA?
Do not use EVKEEZA if you are allergic to evinacumab-dgnb or to any of the ingredients in EVKEEZA. See the end of this leaflet for a complete list of ingredients in EVKEEZA.

Before receiving EVKEEZA, tell your healthcare provider about all of your medical conditions, including if you:

- are pregnant or plan to become pregnant. EVKEEZA may harm your unborn baby. Tell your healthcare provider if you become pregnant while using EVKEEZA. People who are able to become pregnant:
  - Your healthcare provider may do a pregnancy test before you start treatment with EVKEEZA.
  - You should use an effective method of birth control during treatment and for at least 5 months after the last dose of EVKEEZA. Talk with your healthcare provider about birth control methods that you can use during this time.
- are breastfeeding or plan to breastfeed. It is not known if EVKEEZA passes into your breast milk. You and your healthcare provider should decide if you will receive EVKEEZA or breastfeed.

Tell your healthcare provider about all of the medicines you take, including prescription and over-the-counter medicines, vitamins, and herbal supplements.

How will I receive EVKEEZA?

- Your healthcare provider will give you EVKEEZA into your veins through an intravenous (IV) line over 60 minutes.
- EVKEEZA should be given every month (4 weeks).
- If you miss any infusion appointments, call your healthcare provider as soon as possible to reschedule.
- Your healthcare provider may slow down your infusion rate, temporarily stop, or permanently stop treatment with EVKEEZA if you have certain side effects. See "What are the possible side effects of EVKEEZA?"
- Your healthcare provider may prescribe other cholesterol-lowering medicines, to use with EVKEEZA. Use the other prescribed medicines exactly as your healthcare provider tells you to.

What are the possible side effects of EVKEEZA?
EVKEEZA can cause serious side effects, including:

- Allergic reactions (hypersensitivity), including a severe reaction known as anaphylaxis. Tell your healthcare provider right away if you get any of the following symptoms:

- swelling – mainly of the lips, tongue or throat which makes it difficult to swallow or breathe

- breathing problems or wheezing
- feeling dizzy or fainting

- rash, hives
- itching

The most common side effects of EVKEEZA include:

- symptoms of the common cold
- flu like symptoms

- dizziness
- runny nose

- nausea
- feeling tired or weak

Tell your healthcare provider if you have any side effect that bothers you or that does not go away.
These are not all of the possible side effects of EVKEEZA.
Call your doctor for medical advice about side effects. You may report side effects to FDA at 1-800-FDA-1088.

General information about the safe and effective use of EVKEEZA.
Medicines are sometimes prescribed for purposes other than those listed in a Patient Information leaflet. If you would like more information about EVKEEZA, talk with your healthcare provider. You can ask your healthcare provider for information about EVKEEZA that is written for health professionals.

What are the ingredients in EVKEEZA?
Active ingredient: evinacumab-dgnb
Inactive ingredients: L-arginine hydrochloride, L-histidine, L-histidine monohydrochloride monohydrate, L-proline, polysorbate 80, and Water for Injection, USP.

Manufactured by:
Regeneron Pharmaceuticals, Inc. 777 Old Saw Mill River Road Tarrytown, NY 10591-6707 U.S. License No. 1760
©2025 Regeneron Pharmaceuticals, Inc. All rights reserved.
For more information about EVKEEZA, go to www.EVKEEZA.com or call 1-833-EVKEEZA (833-385-3392)

This Patient Information has been approved by the U.S. Food and Drug Administration.

Revised: September 2025

PRINCIPAL DISPLAY PANEL - 345 mg/2.3 mL Vial Carton

NDC 61755-013-01
Rx only

Evkeeza®
(evinacumab-dgnb)
Injection

345 mg/2.3 mL (150 mg/mL)

For Intravenous Infusion after Dilution

Single-Dose Vial – Discard Unused Portion

Must dilute before use.

Do not use vial if seal is broken or missing.

Do not use after expiration.

Store in the original carton to
protect from light.

PRINCIPAL DISPLAY PANEL - 1200 mg/8 mL Vial Carton

NDC 61755-010-01
Rx only

Evkeeza®
(evinacumab-dgnb)
Injection

1200 mg/8 mL (150 mg/mL)

For Intravenous Infusion after Dilution

Single-Dose Vial – Discard Unused Portion

Must dilute before use.

Do not use vial if seal is broken or missing.

Do not use after expiration.

Store in the original carton to protect
from light.